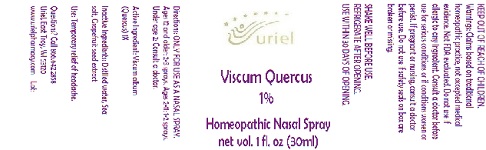 DRUG LABEL: Viscum Quercus 1%
NDC: 48951-9322 | Form: SPRAY
Manufacturer: Uriel Pharmacy Inc.
Category: homeopathic | Type: HUMAN OTC DRUG LABEL
Date: 20180514

ACTIVE INGREDIENTS: VISCUM ALBUM FRUITING TOP 1 [hp_X]/1 mL
INACTIVE INGREDIENTS: WATER; SODIUM CHLORIDE; CITRUS PARADISI SEED

Viscum Quercus 1%

INDICATIONS AND USAGE

Directions: ONLY FOR USE AS A NASAL SPRAY.

DOSAGE AND ADMINISTRATION

Ages 12 and older: 2-3 sprays. Ages 2-11: 1-2 sprays. Under age 2: Consult a doctor.

Active Ingredient: Viscum album
(Quercus) 1X

Inactive Ingredients: Distilled water, Sea
salt, Grapefruit seed extract

PURPOSE

Use: Temporary relief of headache.

KEEP OUT OF REACH OF CHILDREN.

WARNINGS

Warnings: Claims based on traditional homeopathic practice, not accepted medical evidence. Not FDA evaluated. Do not use if allergic to any ingredient. Consult a doctor before use for serious conditions or if conditions worsen or persist. If pregnant or nursing, consult a doctor before use. Do not use if safety seals on box are broken or missing.

SHAKE WELL BEFORE USE.
REFRIGERATE AFTER OPENING.
USE WITHIN 30 DAYS OF OPENING.

Questions? Call 866.642.2858
Uriel, East Troy, WI 53120
www.urielpharmacy.com